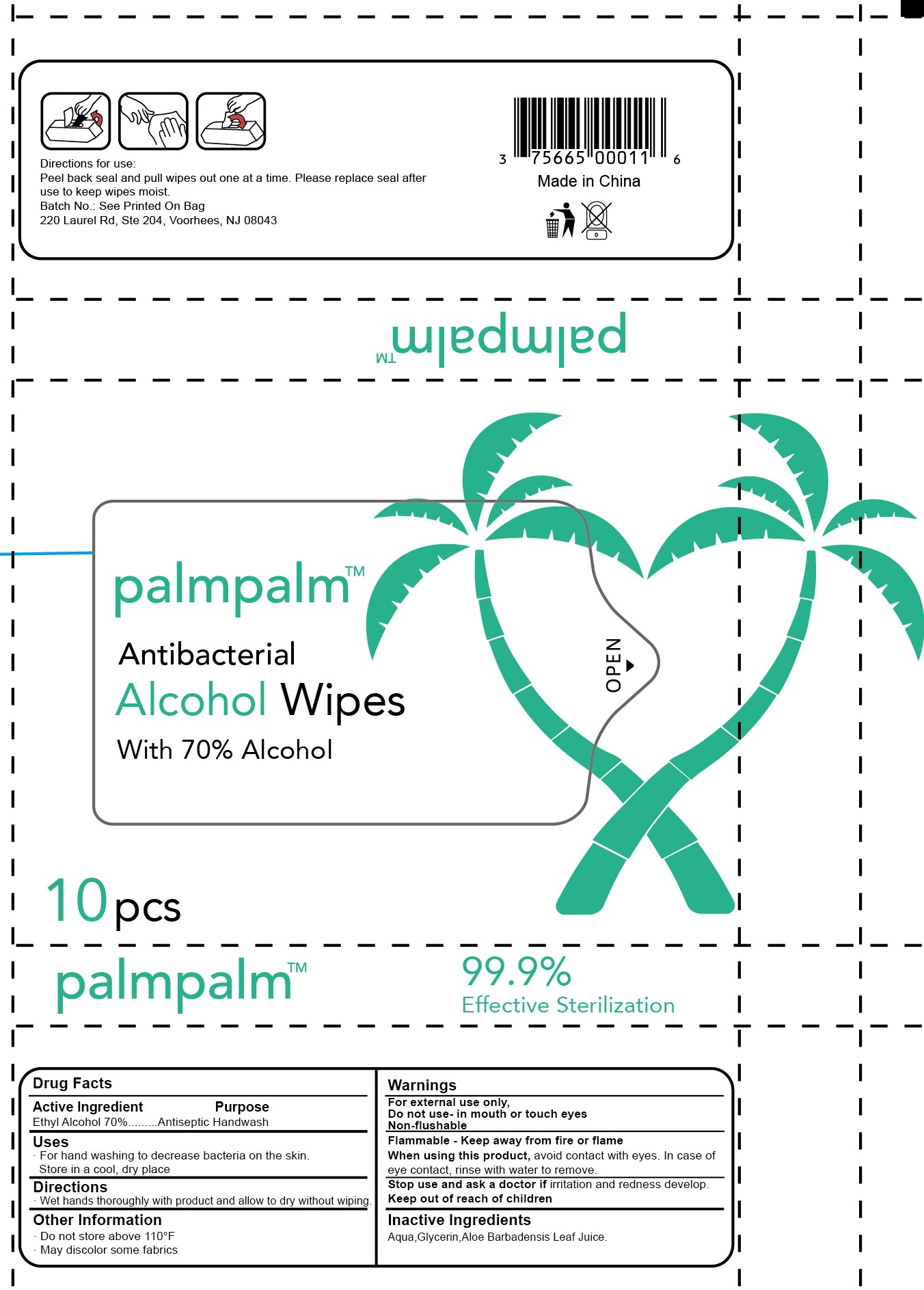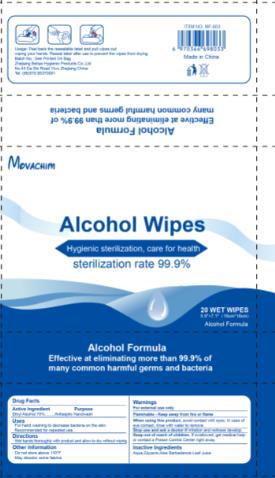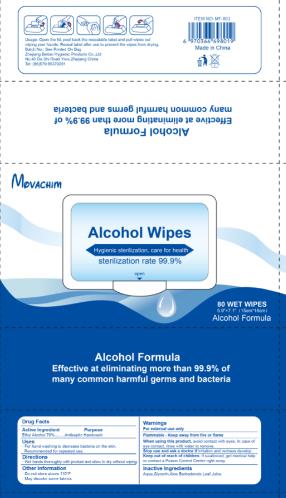 DRUG LABEL: Wet Wipe
NDC: 76906-001 | Form: SWAB
Manufacturer: Zhejiang BeiTao Hygienic Products Co., Ltd.
Category: otc | Type: HUMAN OTC DRUG LABEL
Date: 20241220

ACTIVE INGREDIENTS: ALCOHOL 70 g/100 g
INACTIVE INGREDIENTS: WATER

76906-001 wet wipes70% Alcohol

Active Ingredient

Ethanol 70%

Purpose

Antiseptice Handwash

USE

For hand washing to decrease bacteria on the skin.
Recommended for repeated use.

Warning

For external use only
Flammable - Keep away from fire or flame
When using this product, avoid contact with eyes. In case of
eye contact, rinse with water to remove.
Stop use and ask a doctor if irritation and redness develop.

Keep out of reach of children. If swallowed, get medical help
or contact a Poison Control Center right away.

Directions

. Wet hands thoroughly with product and allow to dry without wiping.

Inactive ingredients

Aqua

PACKAGE LABEL

NDC 76906-001-02

NDC 76906-001-06

NDC 76906-001-13